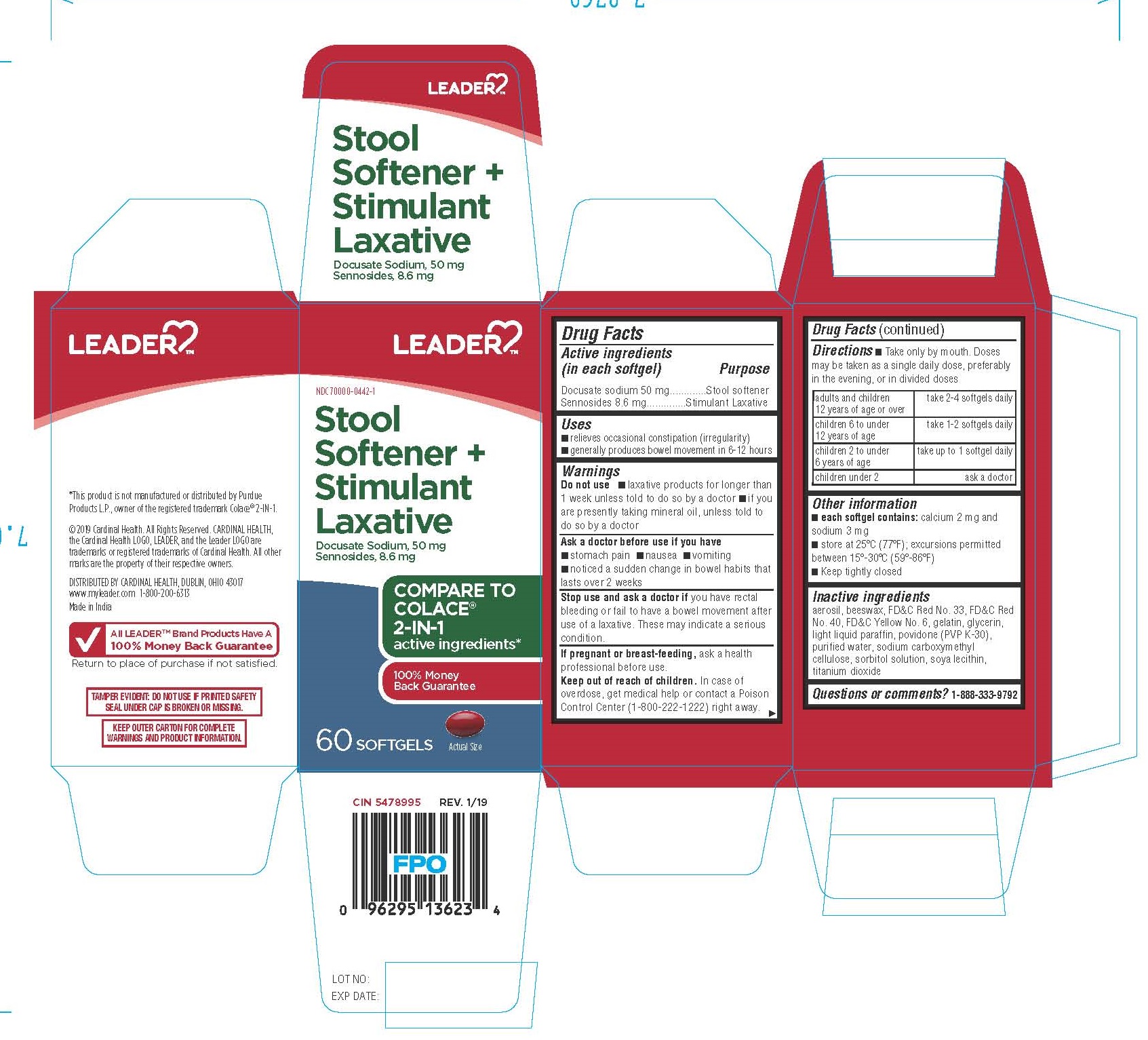 DRUG LABEL: STOOL SOFTENER AND STIMULANT LAXATIVE
NDC: 70000-0442 | Form: CAPSULE, GELATIN COATED
Manufacturer: Cardinal Health
Category: otc | Type: HUMAN OTC DRUG LABEL
Date: 20250818

ACTIVE INGREDIENTS: DOCUSATE SODIUM 50 mg/1 1; SENNOSIDES 8.6 mg/1 1
INACTIVE INGREDIENTS: POVIDONE K30; WATER; CARBOXYMETHYLCELLULOSE SODIUM; SORBITOL; LECITHIN, SOYBEAN; TITANIUM DIOXIDE; SILICON DIOXIDE; YELLOW WAX; D&C RED NO. 33; FD&C RED NO. 40; GELATIN; GLYCERIN; LIGHT MINERAL OIL

Stool Softener + Stimulant Laxative

DRUG FACTS

Purpose
Stool softener
Stimulant Laxative

Active ingredients
(in each softgel)
Docusate sodium 50 mg
Sennosides 8.6 mg

Uses

- relieves occasional constipation (irregularity)
- generally produces bowel movement in 6-12 hours

Warnings

Do not use

- laxative products for longer than 1 week unless told to do so by a doctor
- if you are presently taking mineral oil, unless told to do so by a doctor

Ask a doctor before use if you have

- stomach pain
- nausea
- vomiting
- noticed a sudden change in bowel habits that lasts over 2 weeks

Stop use and ask a doctor if you have rectal bleeding or fail to have a bowel movement after use of a laxative. These may indicate a serious condition.

PREGNANCY OR BREAST FEEDING

If pregnant or breast-feeding, ask a health professional before use.

Keep out of reach of children. In case of overdose, get medical help or contact a Poison Control Center (1800-222-1222) right away.

Directions

- Take only by mouth. Doses may be taken as a single daily dose, preferably in the evening, or in divided doses

adults and children 12 years of age or over | take 2-4 softgels daily
children 6 to under 12 years of age | take 1-2 softgels daily
children 2 to under 6 years of age | take upto 1 softgel daily
children under 2 | ask a doctor

Other information

- each softgel contains: calcium 2 mg and sodium 3 mg
- store at 25°C (77°F); excursions permitted between 15°-30°C (59°-86°F)
- Keep tightly closed

Inactive ingredients

Aerosil, beeswax, FD&C Red No.33, FD&C Red No.40, gelatin, glycerin, light liquid paraffin, povidone (PVP K-30), purified water, sodium carboxymethylcellulose, sorbitol solution, soya lecithin, titanium dioxide

Questions or Comments?

1-888-333-9792

*This product is not manufactured or distributed by Purdue
Products L.P., owner of the registered trademark Colace® 2-IN-1.

© 2019 Cardinal Health. All Rights Reserved. CARDINAL HEALTH,
the Cardinal Health LOGO, LEADER, and the Leader LOGO are
trademarks or registered trademarks of Cardinal Health. All other
marks are the property of their respective owners.

DISTRIBUTED BY CARDINAL HEALTH, DUBLIN, OHIO 43017
www.myleader.com 1-800-200-6313
Made in India

All LEADER™ Brand Products Have A
Return to place of purchase if not satisfied.
100% Money Back Guarantee

TAMPER EVIDENT: DO NOT USE IF PRINTED SAFETY
SEAL UNDER CAP IS BROKEN OR MISSING.

KEEP OUTER CARTON FOR COMPLETE
WARNINGS AND PRODUCT INFORMATION

PRINCIPAL DISPLAY PANEL - 60 Capsule Bottle Carton

Leader™

NDC 70000-0442-1

Stool
Softener +
Stimulant
Laxative

Docusate Sodium, 50 mg
Sennosides, 8.6 mg

COMPARE TO
COLACE®
2-IN-1
active ingredients*

100% Money
Back Guarantee

60 SOFTGELS

Actual Size